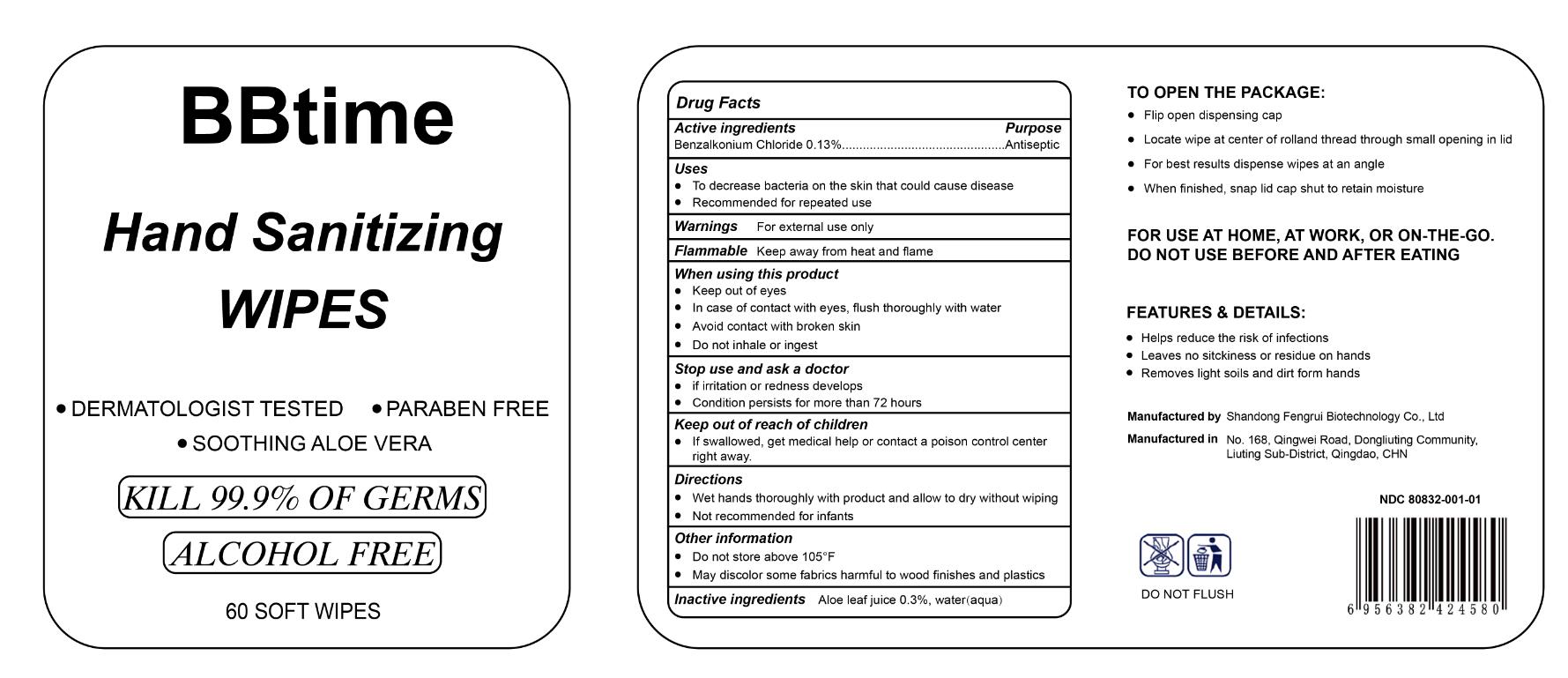 DRUG LABEL: BBtime Hand Sanitizing Wipes
NDC: 80832-001 | Form: CLOTH
Manufacturer: Qingdao Fengrui Biotechnology Co., Ltd.
Category: otc | Type: HUMAN OTC DRUG LABEL
Date: 20201019

ACTIVE INGREDIENTS: BENZALKONIUM CHLORIDE 13 g/100 g
INACTIVE INGREDIENTS: ALOE; WATER

ACTIVE INGREDIENT

Benzalkonium Chloride 0.13%

PURPOSE

Antiseptic

Uses

- To decrease bacteria on the skin that could cause disease
- Recommended for repeated use

Warnings: For external use only

Flammable: Keep away from heat and flame

WHEN USING

Keep out of eyes

In case of contact with eyes, flush thoroughly with water

Avoid contact with broken skin

Do not inhale or ingest

Stop use and ask a doctor

- if irritation or redness develops
- Condition persists for more than 72 hours

KEEP OUT OF REACH OF CHILDREN

If swallowed, get medical help or contact a poison control center right away

DOSAGE AND ADMINISTRATION

- Wet hands thoroughly with product and allow to dry without wiping
- Not recommended for infants

Other information

- Do not store above 105°F
- May discolor some fabrics harmful to wood finishes and plastics

INACTIVE INGREDIENT

Aloe leaf juice 0.3%, water(aqua)

DERMATOLOGIST TESTED

PARABEN FREE

SOOTHING ALOE VERA

KILL 99.9% OF GERMS

ALCOHOL FREE

60 SOFT WIPES

TO OPEN PACKAGE

Flip open dispensing cap
Locate wipe at center of rolland thread through small opening in lid
For best results dispense wipes at angle
When finished, snap lid acap shut to retain moisture

For use at home, at work, ro on-the-go.

DO NOT USE BEFORE AND AFTER EATING

Feature & details:

• Helps reduce the risk of infections

• Leaves no stickiness or residue on hands

• Removes light soils and dirt from hands

Manufactured by Shandong Fengrui Biotechnology Co., Ltd.

Manufactured in No.168, Qingwei Road, Dongliuting Community, Liuting sub-district, Qingdao, CHN

DO NOT FLUSH

NDC 80832-001-01

PACKAGE LABEL

NDC 80832-001-01